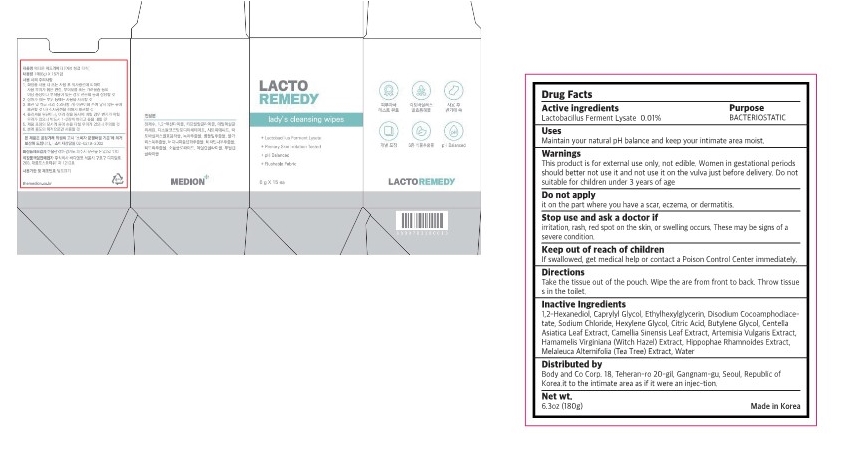 DRUG LABEL: LACTO REMEDY ladys cleansing wipes
NDC: 82892-302 | Form: SWAB
Manufacturer: Body and Co Corp.
Category: otc | Type: HUMAN OTC DRUG LABEL
Date: 20230424

ACTIVE INGREDIENTS: LIMOSILACTOBACILLUS FERMENTUM 0.01 g/100 g
INACTIVE INGREDIENTS: HAMAMELIS VIRGINIANA TOP; HIPPOPHAE RHAMNOIDES FRUIT; HEXYLENE GLYCOL; 1,2-HEXANEDIOL; DISODIUM COCOAMPHODIACETATE; SODIUM CHLORIDE; ETHYLHEXYLGLYCERIN; CENTELLA ASIATICA LEAF; ARTEMISIA VULGARIS WHOLE; MELALEUCA ALTERNIFOLIA WHOLE; WATER; GREEN TEA LEAF; CAPRYLYL GLYCOL; CITRIC ACID MONOHYDRATE; BUTYLENE GLYCOL

LACTO REMEDY lady's cleansing wipes 82892-302

Active ingredients

Lactobacillus Ferment Lysate 0.01%

purpose

BACTERIOSTATIC

use

Maintain your natural pH balance and keep your intimate area moist.

warnings

Do not suitable for children under 3 years of age.

Do not apply it on the part where you have a scar, eczema, or dermatitis.

warnings

Women in gestational periods should better not use it and not use it on the vulva just before delivery.

warnings

Stop use and ask a doctor if
irritation, rash, red spot on the skin, or swelling occurs. These may be signs of a severe condition.

warnings

Keep out of reach of children
If swallowed, get medical help or contact a Poison Control Center immediately

Directions

Take the tissue out of the pouch. Wipe the are from front to back. Throw tissue s in the toilet.

Inactive ingredient

1,2-Hexanediol, Caprylyl Glycol, Ethylhexylglycerin, Disodium Cocoamphodiace- tate, Sodium Chloride, Hexylene Glycol, Citric Acid, Butylene Glycol, Centella Asiatica Leaf Extract, Camellia Sinensis Leaf Extract, Artemisia Vulgaris Extract, Hamamelis Virginiana (Witch Hazel) Extract, Hippophae Rhamnoides Extract, Melaleuca Alternifolia (Tea Tree) Extract, Water

warnings

This product is for external use only, not edible.

label